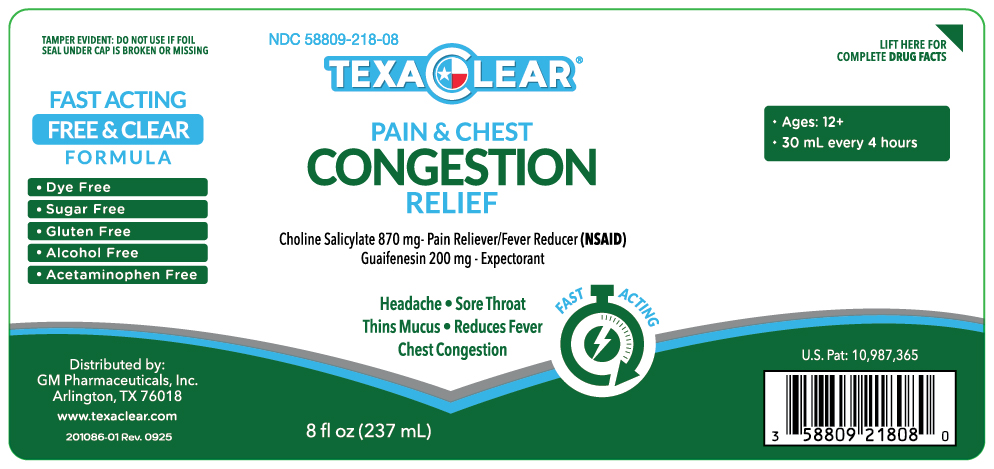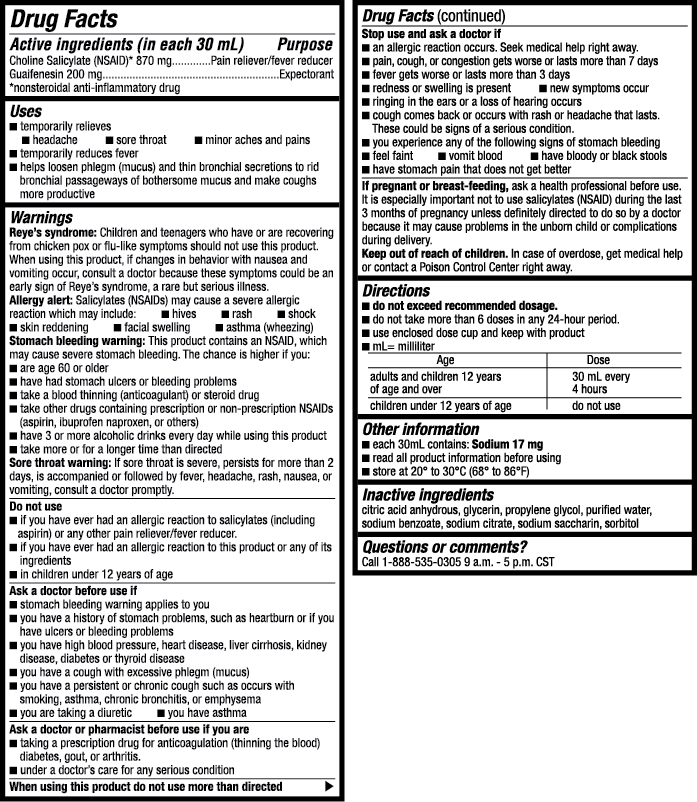 DRUG LABEL: TexaClear Pain and Chest Congestion Relief
NDC: 58809-218 | Form: LIQUID
Manufacturer: GM Pharmaceuticals, INC
Category: otc | Type: HUMAN OTC DRUG LABEL
Date: 20251013

ACTIVE INGREDIENTS: GUAIFENESIN 200 mg/30 mL; CHOLINE SALICYLATE 870 mg/30 mL
INACTIVE INGREDIENTS: PROPYLENE GLYCOL; WATER; SODIUM CITRATE; SACCHARIN SODIUM; SORBITOL; EDETATE DISODIUM; GLYCERIN

TexaClear Pain & Chest Congestion Relief

TexaClear Pain & Chest Congestion Relief

(Choline Salicylate, Guaifenesin)

NDC: 58809-218-08

GM Pharmaceuticals, Inc.

Drug Facts

Active ingredients (in each 30 mL)

Choline Salicylate (NSAID)* 870 mg

Guaifenesin 200 mg

*nonsteroidal anti-inflammatory drug

Purpose

Pain reliever / fever reducer

Expectorant

Uses

- temporarily relieves
  - headache
  - sore throat
  - minor aches and pains
- temporarily reduces fever
- helps loosen phlegm (mucus) and thin bronchial secretions to rid bronchial passageways of bothersome mucus and make coughs more productive

Warnings

Reye’s syndrome:Children and teenagers who have or are recovering from chicken pox or flu-like symptoms should not use this product. When using this product, if changes in behavior with nausea and vomiting occur, consult a doctor because these symptoms could be an early sign of Reye’s syndrome, a rare but serious illness.

Allergy alert:Salicylates (NSAIDs) may cause a severe allergic reaction which may include:

- hives
- rash
- shock
- skin reddening
- facial swelling
- asthma (wheezing)

Stomach bleeding warning: This product contains an NSAID, which may cause severe stomach bleeding. The chance is higher if you:

- are age 60 or older
- have had stomach ulcers or bleeding problems
- take a blood thinning (anticoagulant) or steroid drug
- take other drugs containing prescription or non-prescription NSAIDs (aspirin, ibuprofen naproxen, or others)
- have 3 or more alcoholic drinks every day while using this product
- take more or for a longer time than directed

Sore throat warning: If sore throat is severe, persists for more than 2 days, is accompanied or followed by fever, headache, rash, nausea, or vomiting, consult a doctor promptly.

Do not use

- if you have ever had an allergic reaction to salicylates (including aspirin) or any other pain reliever/ fever reducer.
- if you have ever had an allergic reaction to this product or any of its ingredients
- in children under 12 years of age

Ask a doctor before use if

- stomach bleeding warning applies to you
- you have a history of stomach problems, such as heartburn or if you have ulcers or bleeding problems
- you have high blood pressure, heart disease, liver cirrhosis, kidney disease, diabetes or thyroid disease
- you have a cough with excessive phlegm (mucus)
- you have a persistent or chronic cough such as occurs with smoking, asthma, chronic bronchitis, or emphysema
- you are taking a diuretic
- have asthma

Ask a doctor or pharmacist before use if you are

- taking a prescription drug for anticoagulation (thinning the blood) diabetes, gout, or arthritis.
- under a doctor’s care for any serious condition

Stop use and ask a doctor if

- an allergic reaction occurs. Seek medical help right away.
- pain, cough, or nasal congestion gets worse or lasts more than 7 days
- fever gets worse or lasts more than 3 days
- redness or swelling is present
- new symptoms occur
- ringing in the ears or a loss of hearing occurs
- cough comes back or occurs with rash or headache that lasts. These could be signs of a serious condition.
- you experience any of the following signs of stomach bleeding
  - feel faint
  - vomit blood
  - have bloody or black stools
  - have stomach pain that does not get better

If pregnant or breast-feeding,

ask a health professional before use. It is especially important not to use salicylates (NSAID) during the last 3 months of pregnancy unless definitely directed to do so by a doctor because it may cause problems in the unborn child or complications during delivery.

Keep out of reach of children.

In case of overdose, get medical help or contact a Poison Control Center right away.

Directions

- do not exceed recommended dosage.
- do not take more than 6 doses in any 24-hour period.
- use enclosed dose cup and keep with product
- mL= milliliter

Age | Dose
adults and children 12 years of age and over: | 30 mL every 4 hours
children under 12 years of age: | do not use.

Other information

- each 30mL contains: Sodium 17 mg
- read all product information before using
- store at 68° to 86°F (20° to 30°C)

Inactive ingredients

citric acid anhydrous, glycerin, propylene glycol, purified water, sodium benzoate, sodium citrate, sodium saccharin, sorbitol

Questions or comments?

Call 1-888-535-0305 9 a.m.-5 p.m. CST

PRINCIPAL DISPLAY PANEL

NDC 58809-218-08
TexaClear Pain & Chest Congestion Relief
8 fl oz(237 mL)